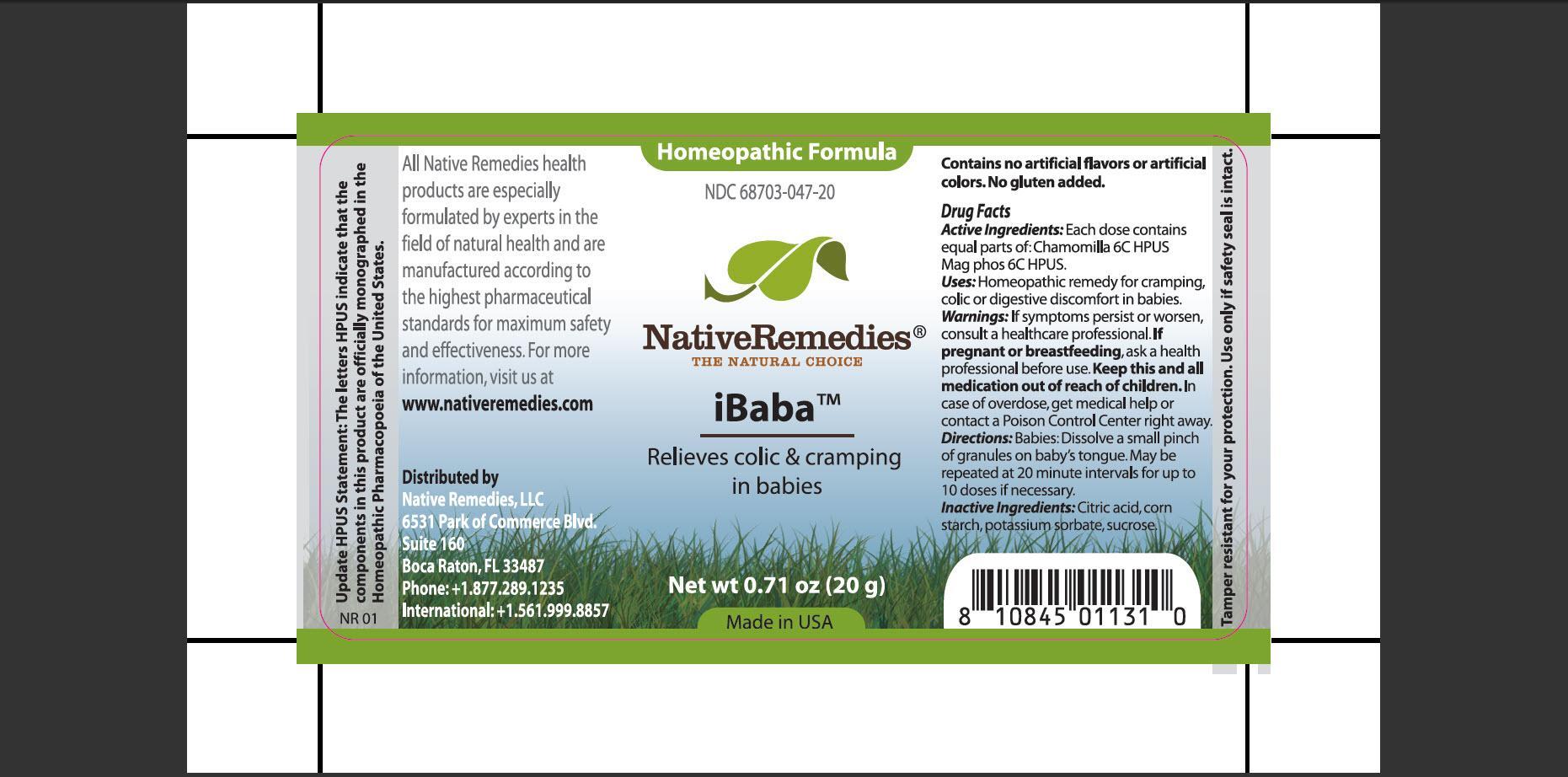 DRUG LABEL: iBaba
                
NDC: 68703-047 | Form: GRANULE
Manufacturer: Native Remedies, LLC
Category: homeopathic | Type: HUMAN OTC DRUG LABEL
Date: 20130107

ACTIVE INGREDIENTS: MATRICARIA RECUTITA 6 [hp_C]/40 mg; MAGNESIUM PHOSPHATE, DIBASIC TRIHYDRATE 6 [hp_C]/40 mg
INACTIVE INGREDIENTS: CITRIC ACID MONOHYDRATE; STARCH, CORN; POTASSIUM SORBATE; SUCROSE

iBaba

PURPOSE

Relieves colic & cramping in babies

ACTIVE INGREDIENT

Active Ingredients: Each dose contains equal parts of:Chamomilla 6C HPUS, Mag phos 6C HPUS

INDICATIONS AND USAGE

Uses: Homeopathic remedy for cramping, colic or digestive discomfort in babies.

WARNINGS

Warnings: If symptoms persist or worsen, consult a health care professional.

PREGNANCY OR BREAST FEEDING

If pregnant or breastfeeding, ask a health professional before use.

KEEP OUT OF REACH OF CHILDREN

Keep this and all medication out of reach of children.

OVERDOSAGE

In case of overdose, get medical help or contact a Poison Control Center right away.

DOSAGE AND ADMINISTRATION

Directions: Babies: Dissolve a small pinch of granules on baby's tongue. May be repeated at 20 minute intervals for up to 10 doses if necessary.

INACTIVE INGREDIENT

Inactive Ingredients: Citric acid, corn starch, potassium sorbate, sucrose.

PATIENT COUNSELING INFORMATION

Update HPUS Statement: The letters HPUS indicate that the components in this product are officially monographed in the Homeopathic Pharmacopoeia of the United States.

All Native Remedies health products are especially formulated by experts in the field of natural health and are manufactured according to the highest pharmaceutical standards for maximum safety and effectiveness. For more information, visit us at www.nativeremedies.com

Distributed by
Native Remedies, LLC
6531 Park of Commerce Blvd.
Suite 160
Boca Raton, Fl 33487
Phone:+1.877.289.1235
International:+1.561.999.8857

Contains no artificial flavors or artificial colors. No gluten added.

STORAGE AND HANDLING

Tamper resistant for your protection. Use only if safety seal is intact.